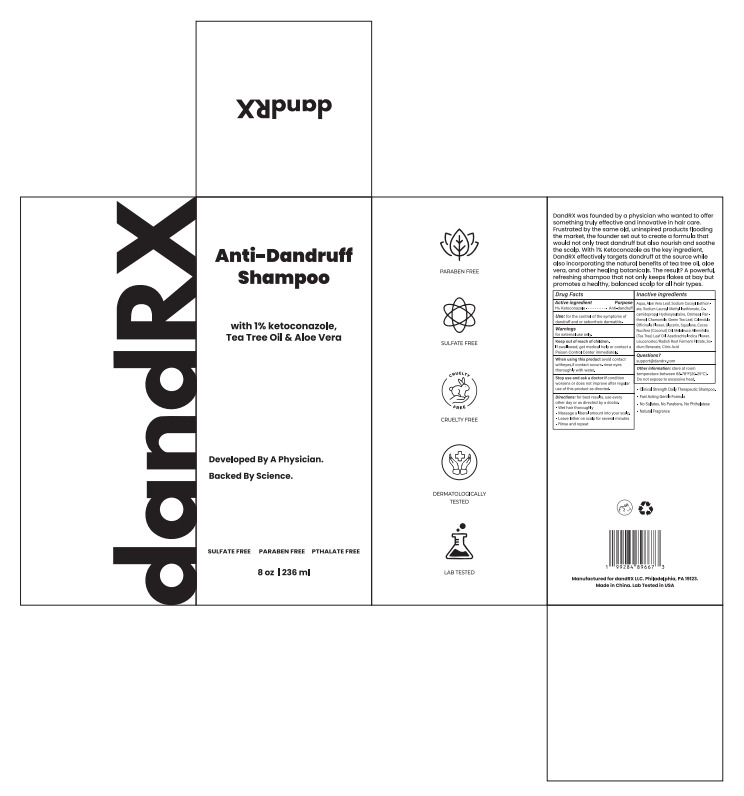 DRUG LABEL: dandRX 1% Ketoconazole Anti-Dandruff
NDC: 85521-001 | Form: LIQUID
Manufacturer: dandRX LLC
Category: otc | Type: HUMAN OTC DRUG LABEL
Date: 20250408

ACTIVE INGREDIENTS: KETOCONAZOLE 1 g/100 mL
INACTIVE INGREDIENTS: GLYCERIN; LEUCONOSTOC/RADISH ROOT FERMENT FILTRATE; AQUA; SODIUM COCOYL ISETHIONATE; SODIUM LAUROYL METHYL ISETHIONATE; COCAMIDOPROPYL HYDROXYSULTAINE; OATMEAL; PANTHENOL; CHAMOMILE; GREEN TEA LEAF; CALENDULA OFFICINALIS FLOWER; SODIUM BENZOATE; COCOS NUCIFERA (COCONUT) OIL; MELALEUCA ALTERNIFOLIA (TEA TREE) LEAF OIL; AZADIRACHTA INDICA FLOWER; SQUALANE; ALOE VERA LEAF; CITRIC ACID

85521-001
dandRX 1% Ketoconazole Anti-Dandruff Shampoo

Active Ingredient(s)

KETOCONAZOLE 1%

Purpose

Anti-dandruff

Use

Use: for the control of the symptoms of dandruff and or seborrheic dermatitis.

Warnings

for external use only.

Do not use on open skin wounds

When using this product avoid contact witheyes,if contact occurs. rinse eyes thoroughly with water.

Stop use and ask a doctor if condition worsens or does not improve after regular use of this product as directed.

KEEP OUT OF REACH OF CHILDREN

If swallowed, get medical help or contact a Poison Control Center immediately.

Directions

Directions: for best results, use every other day or as directed by a doctor.

■ Wet hair thoroughly
■ Massage a liberal amount into your scalp.
■ Leave lather on scalp for several minutes
■ Rinse and repeat

Other information

Other information: store at room
temperature between 68-78°F(20-25°C).
Do not expose to excessive heat.

Inactive ingredients

Aqua, Aloe Vera Leaf, Sodium Cocoyl Isethion-ate, Sodium LauroyI Methyl Isethionate, Co-
camidopropyl Hydroxysultaine, Oatmeal, Pan-thenol, Chamomile, Green Tea Leaf, Calendula
Officinalis Flower, Glycerin, Squalane, Cocos Nucifera (Coconut) Oil, Melaleuca Alternifolia
(Tea Tree) Leaf Oil, Azadirachta Indica Flower, Leuconostoc/Radish Root Ferment Filtrate, So-
dium Benzoate, Citric Acid